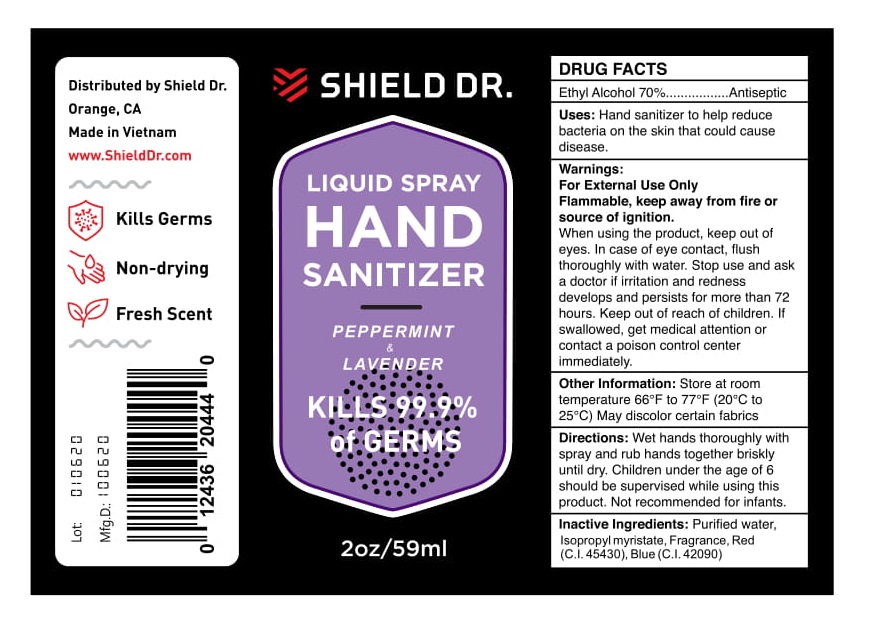 DRUG LABEL: Shield Dr.
NDC: 79633-301 | Form: LIQUID
Manufacturer: MEDIPHARCO PHARMACEUTICAL JOINT STOCK COMPANY
Category: otc | Type: HUMAN OTC DRUG LABEL
Date: 20200820

ACTIVE INGREDIENTS: ALCOHOL 70 mL/100 mL
INACTIVE INGREDIENTS: FD&C BLUE NO. 1; LAVENDER OIL; FD&C RED NO. 3; ISOPROPYL MYRISTATE; WATER; PEPPERMINT OIL

ACTIVE INGREDIENT

Ethyl Alcohol 70%

INACTIVE INGREDIENT

Purified water

Isopropyl myristate

Peppermint oil

Lavender oil

Red (C.I.45430)

Blue (C.I.42090)

PURPOSE

Antiseptic

KEEP OUT OF REACH OF CHILDREN

If swallowed, get medical attention or contact poison control center immediately

DOSAGE AND ADMINISTRATION

Wet hand thoroughly with spray and rub hand together briskly until dry. Children under the age of 6 should be supervised while using this product. Not recommended for infants.

INDICATIONS AND USAGE

Hand sanitizer to help reduce bacteria on the skin it could cause disease

WARNINGS

For external use only.

Flammable, keep away from fire or source of ignition.

STORAGE AND HANDLING

Store at room temperature 66o F to 77oF (20oC to 25oC)

PACKAGE LABEL

59ml NDC: 79633-301-59